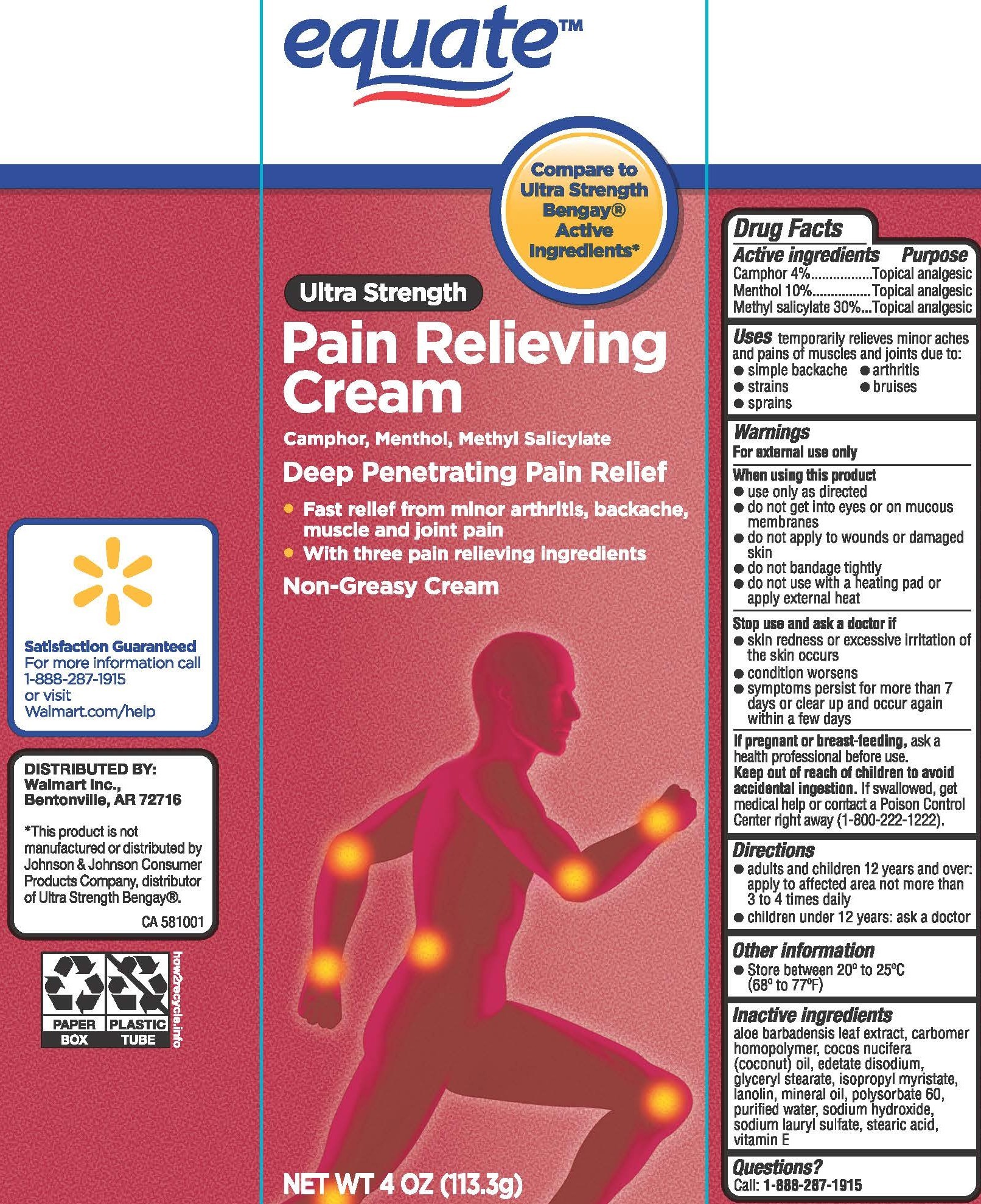 DRUG LABEL: Equate Pain Relieving
NDC: 49035-700 | Form: CREAM
Manufacturer: Wal-Mart Stores Inc
Category: otc | Type: HUMAN OTC DRUG LABEL
Date: 20260119

ACTIVE INGREDIENTS: CAMPHOR (SYNTHETIC) 40 mg/1 g; MENTHOL, UNSPECIFIED FORM 100 mg/1 g; METHYL SALICYLATE 300 mg/1 g
INACTIVE INGREDIENTS: ALOE VERA LEAF; CARBOMER HOMOPOLYMER, UNSPECIFIED TYPE; COCONUT OIL; EDETATE DISODIUM; GLYCERYL MONOSTEARATE; ISOPROPYL MYRISTATE; LANOLIN; MINERAL OIL; POLYSORBATE 60; WATER; SODIUM HYDROXIDE; STEARIC ACID; .ALPHA.-TOCOPHEROL; SODIUM LAURYL SULFATE

Drug Facts - Equate Pain Relieving Ultra Strength

Active ingredients

Camphor 4%

Menthol 10%

Methyl salicylate 30%

Purpose

Camphor - Topical analgesic

Menthol - Topical analgesic

Methyl salicylate - Topical analgesic

Uses

temporarily relieves minor aches and pains of muscles and joints due to:

- simple backache
- arthritis
- strains
- bruises
- sprains

Warnings

For external use only

When using this product

- use only as directed
- do not get into eyes or on mucous membranes
- do not apply to wounds or damaged skin
- do not bandage tightly
- do not use with heating pad or apply external heat

Stop use and ask a doctor if

- skin redness or excessive irritation of the skin occurs
- condition worsens
- symptoms persist for more than 7 days or clear up and occur again within a few days

If pregnant or breast-feeding,

ask a health professional before use.

Keep out of reach of children to avoid accidental ingestion.

If swallowed, get medical help or contact a Poison Control Center right away.

Directions

- adults and children 12 years and over: apply to affected area not more than 3 to 4 times daily
- children under 12 years: ask a doctor

Inactive ingredients

aloe barbadensis leaf extract, carbomer homopolymer, cocos nucifera (coconut) oil, edetate disodium, glyceryl stearate, isopropyl myristate, lanolin, mineral oil, polysorbate 60, purified water, sodium hydroxide, sodium lauryl sulfate, stearic acid, vitamin E

Questions?

Call: 1-888-287-1915